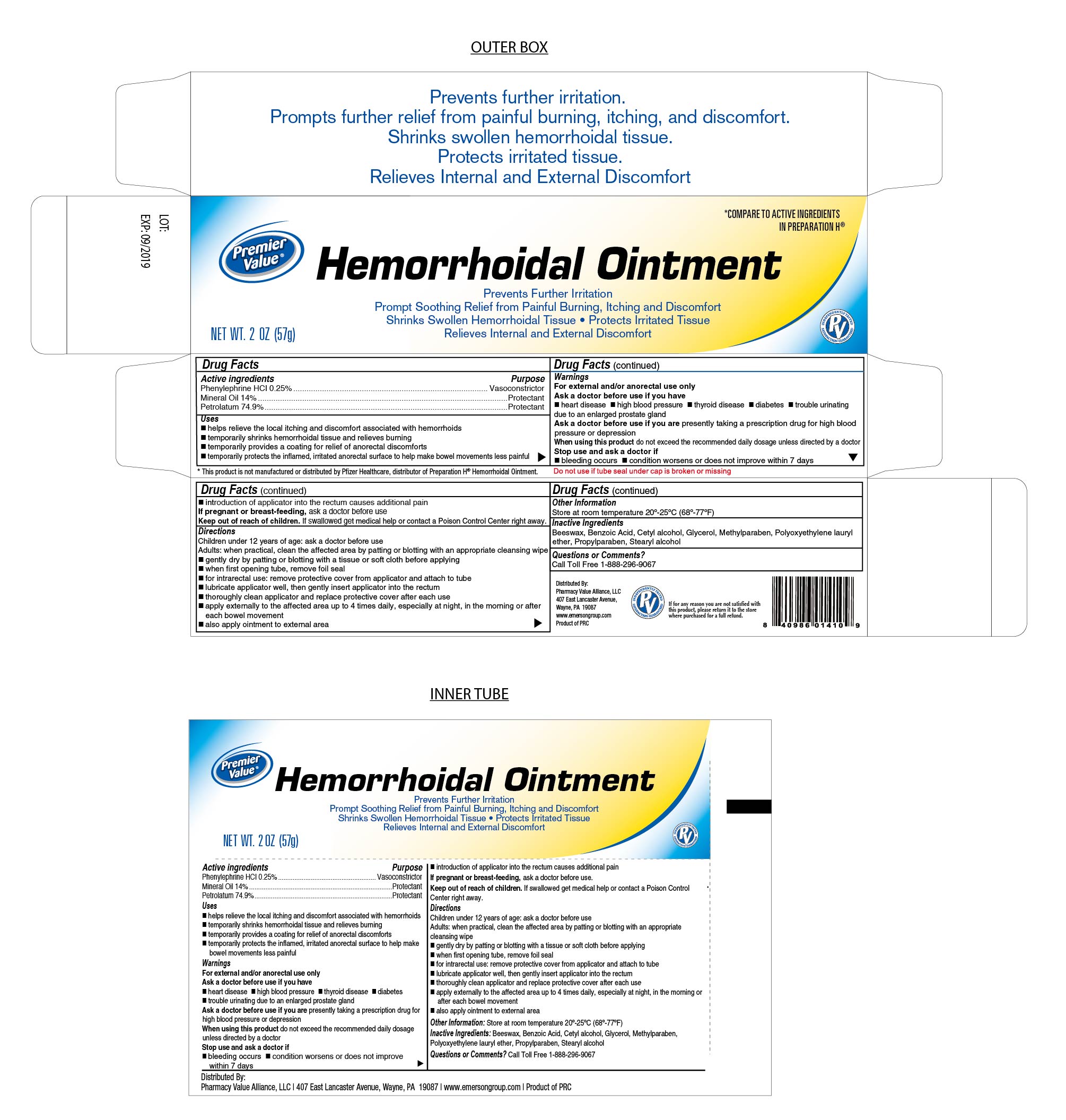 DRUG LABEL: HemorrhoidalOintment
NDC: 68016-528 | Form: OINTMENT
Manufacturer: Pharmacy Value Alliance, LLC
Category: otc | Type: HUMAN OTC DRUG LABEL
Date: 20241220

ACTIVE INGREDIENTS: MINERAL OIL 14 g/100 g; PETROLATUM 74.9 g/100 g; PHENYLEPHRINE HYDROCHLORIDE 0.25 g/100 g
INACTIVE INGREDIENTS: GLYCERIN; LANOLIN; PROPYLPARABEN; THYME OIL; WHITE WAX; PARAFFIN; METHYLPARABEN

Hemorrhoidal Ointment

Active Ingredient

Phenylephrine HCI 0.25%

Purpose

Vasoconstrictor

Active Ingredient

Mineral Oil 14%

Purpose

Protectant

Active Ingredient

Petrolatum 74.9%

Purpose

Protectant

Uses

- Helps relieve the local itching and discomfort associated with hemorrhoids
- Temporarily shrinks hemorrhoidal tissue and relieves burning
- Temporarily provides a coating for relief of anorectal discomforts
- Temporarily protects the inflamed, irritated anorectal surface to help make bowel movements less painful

Warnings

For External and/or anorectal use only

Ask doctor before use if you have

- heart disease
- high blood pressure
- thyroid disease
- diabetes
- trouble urinating due to an enlarged prostate gland

Ask doctor before use if you are presently taking a prescription drug for high blood pressure or depression

When using this product do not exceed the recommended daily dosage unless directed by a doctor

Stop Use and Ask Doctor if

- bleeding occurs
- condition worsens or does not improve within 7 days
- introduction of applicator into the rectum causes additional pain

If Pregnant or breast-feeding

Ask a doctor before use

Keep out of reach of children

If swallowed get medical help or contact a Poison Control Center right away.

Directions

Children under 12 years of age: ask a doctor before use

Adults: when practical, clean the affected area by patting or blotting with an appropriate cleansing wipe

- gently dry by patting or blotting with a tissue or soft cloth before applying
- when first opening tube, remove foil seal
- for intrarectal use: remove protective cover from applicator into the rectum
- lubricate applicator well, then gently insert applicator into the rectum
- thoroughly clean applicator and replace protective cover after each use
- apply externally to the affected area up to 4 times daily, especially at night, in the morning or after each bowel movement
- also apply ointment to external area

Other Information

Store at room temperature 20°-25°C (68°-77°F)

Inactive Ingredients

Beeswax, benzolc acid, Cetyl alcohol, Glycerol, Methylparaben, Polyoxyethylene lauryl ether, Propylparaben, stearyl alcohol

Distributed by:

Pharmacy Value Alliance, LLC.

407 East Lancaster Avenue

Wayne, PA. 19087

www.emersongroup.com

Product of PRC

Hemorrhoidal Ointment

- Prevents Further Irritation
- Prompt Soothing Relief from Painful Burning, Itching and Discomfort
- Shrinks Swollen Hemorrhoidal Tissue
- Protects Irritated Tissue
- Relieves Internal and External Discomfort